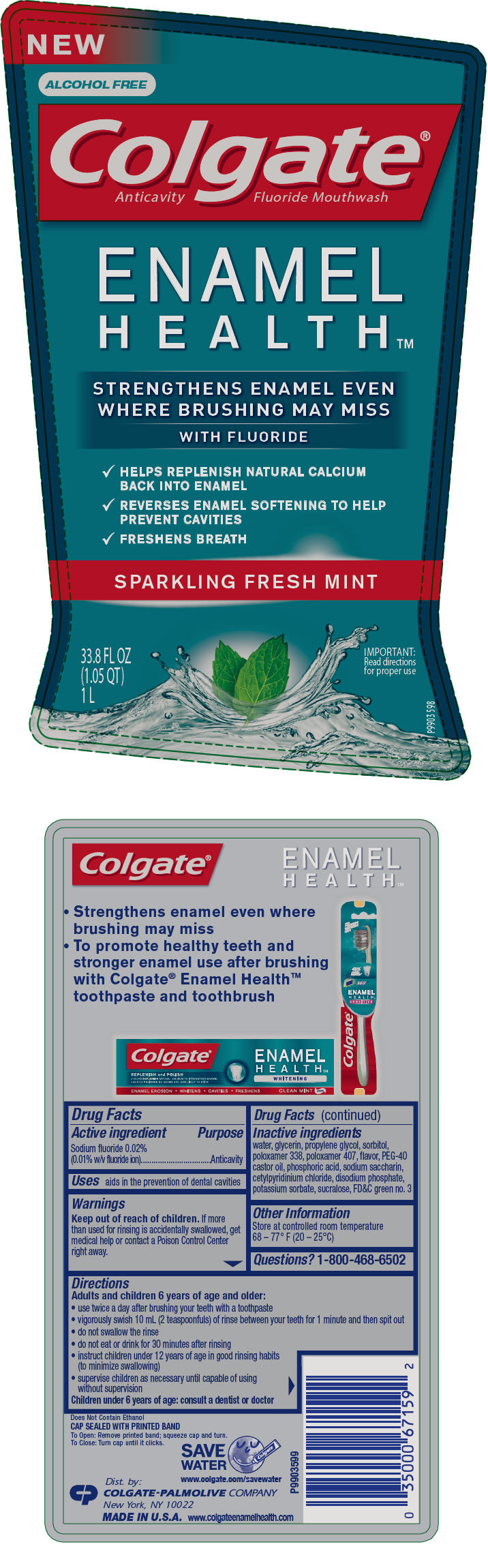 DRUG LABEL: Colgate Enamel Health Mouthwash
NDC: 35000-728 | Form: RINSE
Manufacturer: Colgate-Palmolive Company
Category: otc | Type: HUMAN OTC DRUG LABEL
Date: 20231206

ACTIVE INGREDIENTS: SODIUM FLUORIDE 0.1 mg/1 mL
INACTIVE INGREDIENTS: WATER; GLYCERIN; PROPYLENE GLYCOL; SORBITOL; POTASSIUM SORBATE; CETYLPYRIDINIUM CHLORIDE; SACCHARIN SODIUM; SUCRALOSE; POLOXAMER 407; POLOXAMER 338; SODIUM PHOSPHATE, DIBASIC, ANHYDROUS; PEG-40 CASTOR OIL; PHOSPHORIC ACID; FD&C GREEN NO. 3

Colgate® Enamel Health™ Mouthwash

Drug Facts

Active ingredient

Sodium fluoride 0.02% (0.01% w/v fluoride ion)

Purpose

Anticavity

Uses

aids in the prevention of dental cavities

Warnings

Keep out of reach of children. If more than used for rinsing is accidentally swallowed, get medical help or contact a Poison Control Center right away.

Directions

Adults and children 6 years of age and older:

- use twice a day after brushing your teeth with a toothpaste
- vigorously swish 10 mL (2 teaspoonfuls) of rinse between your teeth for 1 minute and then spit out
- do not swallow the rinse
- do not eat or drink for 30 minutes after rinsing
- instruct children under 12 years of age in good rinsing habits (to minimize swallowing)
- supervise children as necessary until capable of using without supervision

Children under 6 years of age: consult a dentist or doctor

Inactive ingredients

water, glycerin, propylene glycol, sorbitol, poloxamer 338, poloxamer 407, flavor, PEG-40 castor oil, phosphoric acid, sodium saccharin, cetylpyridinium chloride, disodium phosphate, potassium sorbate, sucralose, FD&C green no. 3

Other Information

Store at controlled room temperature 68 – 77° F (20 – 25°C)

Questions?

1-800-468-6502

Dist. by:
COLGATE-PALMOLIVE COMPANY
New York, NY 10022

PRINCIPAL DISPLAY PANEL - 1 L Bottle Label

NEW

ALCOHOL FREE

Colgate®
Anticavity Fluoride Mouthwash

ENAMEL
HEALTH™

STRENGTHENS ENAMEL EVEN
WHERE BRUSHING MAY MISS

WITH FLUORIDE

✓ HELPS REPLENISH NATURAL CALCIUM
  BACK INTO ENAMEL
✓ REVERSES ENAMEL SOFTENING TO HELP
  PREVENT CAVITIES
✓ FRESHENS BREATH

SPARKLING FRESH MINT

33.8 FL OZ
(1.05 QT)
1 L

IMPORTANT:
Read directions
for proper use

P9903598